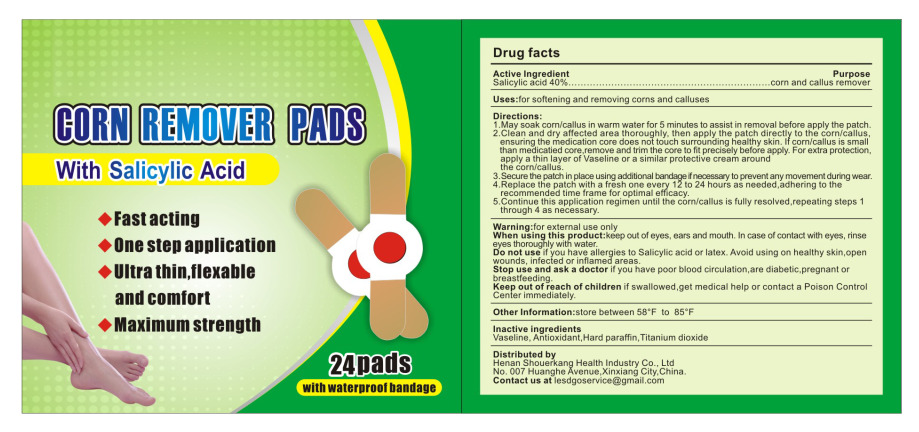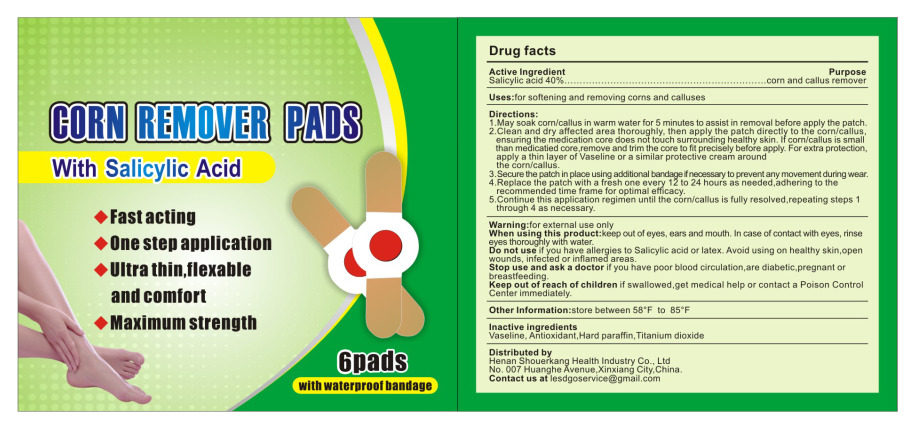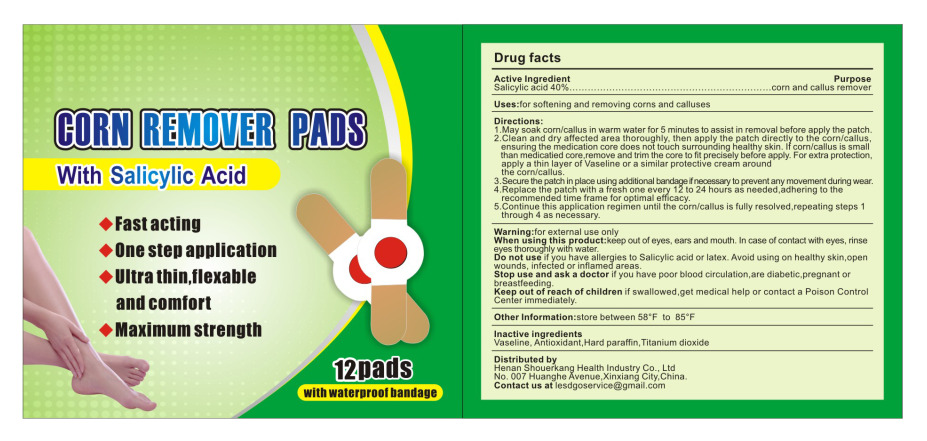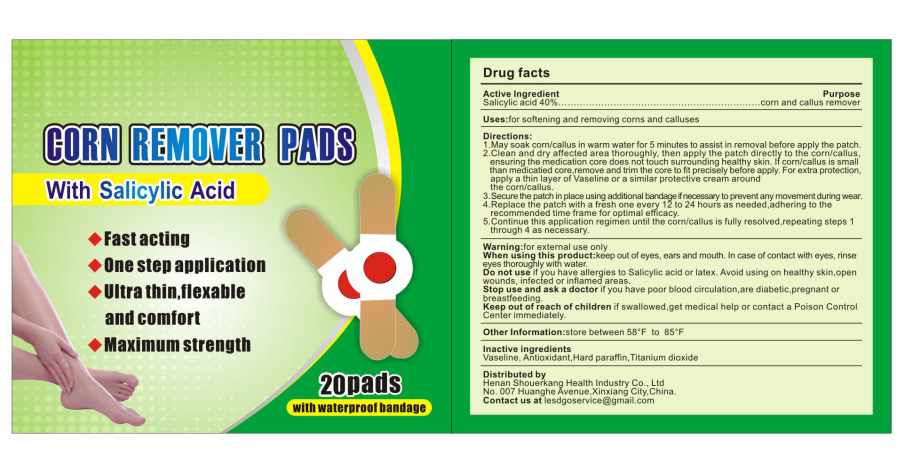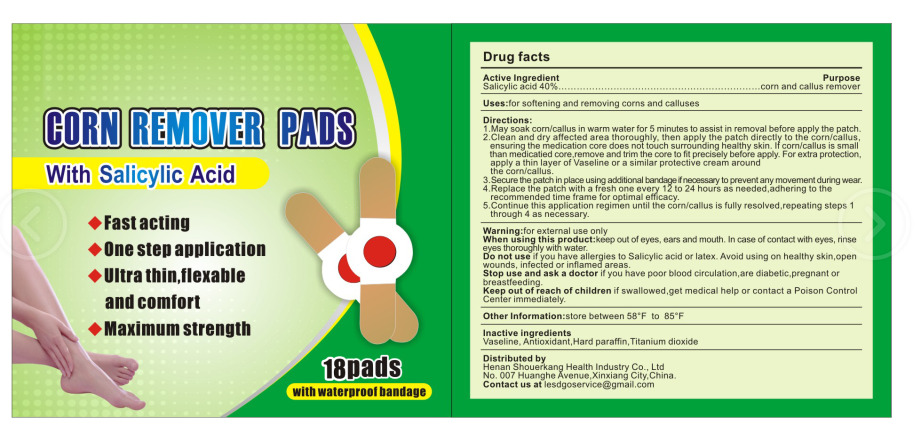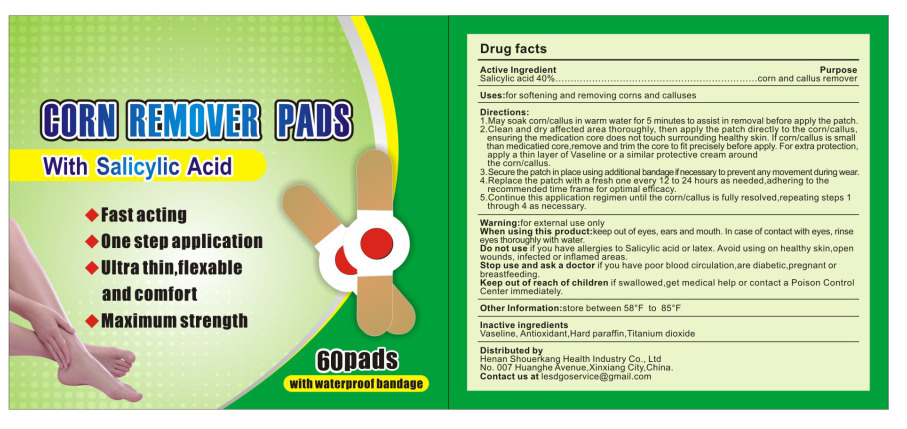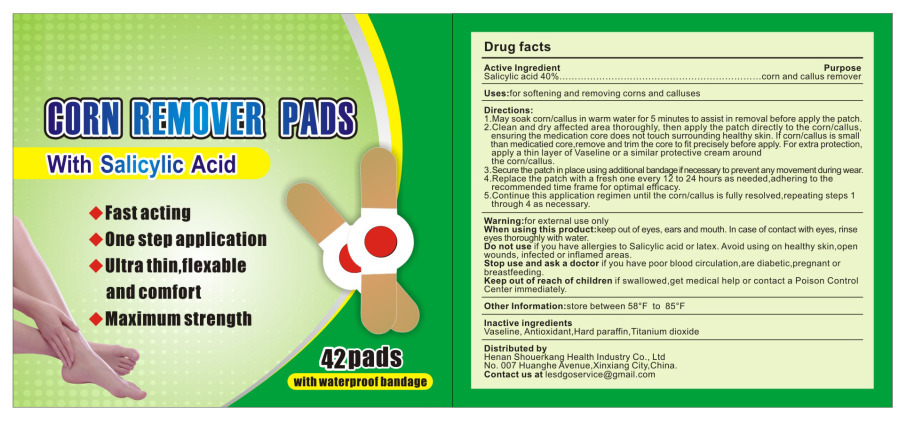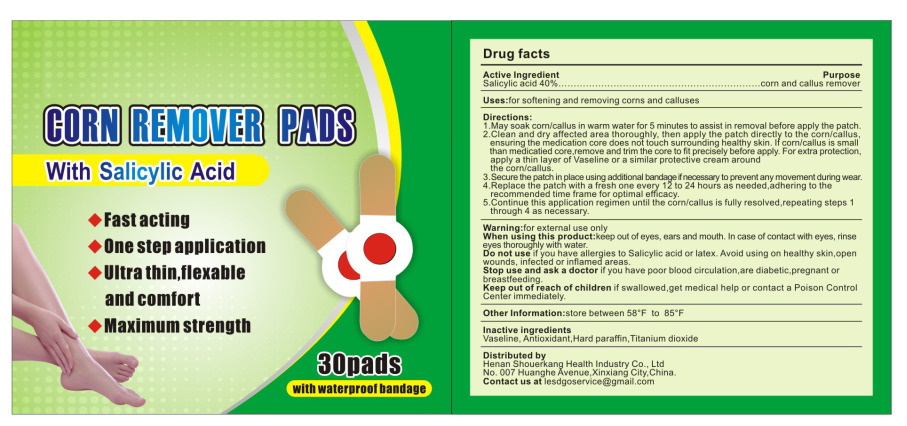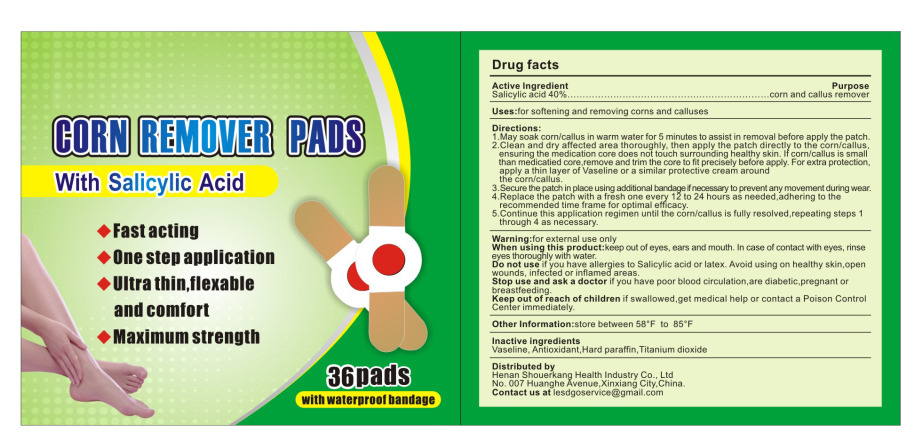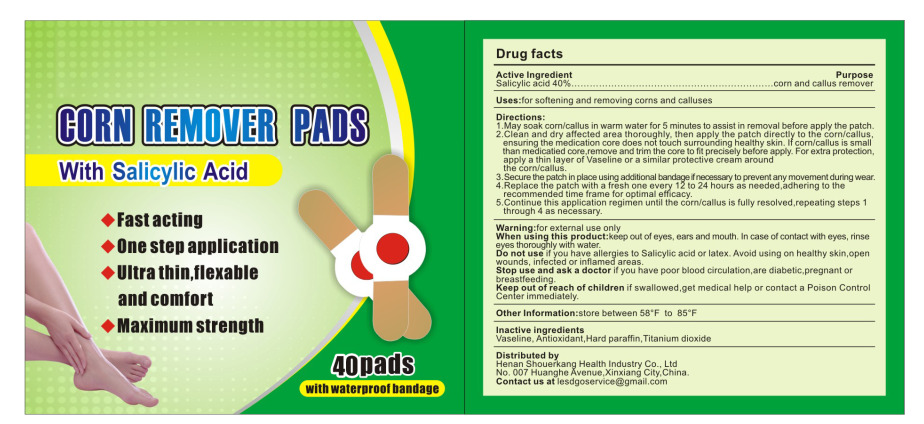 DRUG LABEL: Corn remover pads
NDC: 85056-002 | Form: PASTE
Manufacturer: Henan Shouerkang Health Industry Co., Ltd
Category: otc | Type: HUMAN OTC DRUG LABEL
Date: 20250217

ACTIVE INGREDIENTS: SALICYLIC ACID 40 g/100 1
INACTIVE INGREDIENTS: PETROLATUM; ANTIOXIDANT 119; PARAFFIN; TITANIUM DIOXIDE

85056-002

Active Ingredient(s)

Salicylic acid 40%

Purpose

corn and callus remover

Use

Uses:for softening and removing corns and calluses

Warnings

For external use only.

Do not use if you have allergies to Salicylic acid or latex. Avoid using on healthy skin,open
wounds, infected or inflamed areas.

When using this product:keep out of eyes, ears and mouth. In case of contact with eyes, rinse
eyes thoroughly with water.

Stop use and ask a doctor if you have poor blood circulation, are diabetic,pregnant or
breastfeeding.

Keep out of reach of children if swallowed ,get medical help or contact a Poison Control
Center immediately.

Directions

1.May soak corn/callus in warm water for 5 minutes to assist in removal before apply the patch.
2.Clean and dry affected area thoroughly, then apply the patch directly to the corn/callus,
ensuring the medication core does not touch surrounding healthy skin. If corn/callus is small
than medicatied core,remove and trim the core to fit precisely before apply. For extra protection,
apply a thin layer of Vaseline or a similar protective cream around the corn/callus.
3. Secure the patch in place using additional bandage ifnecessary to prevent any movement during wear.
4.Replace the patch with a fresh one every 12 to 24 hours as needed, adhering to the recommended time frame for optimal efficacy.
5.Continue this application regimen until the corn/callus is fully resolved,repeating steps 1 through 4 as necessary.

Other information

store between 58°F to 85°F

Inactive ingredients

Vaseline, Antioxidant, Hard paraffin, Titanium dioxide